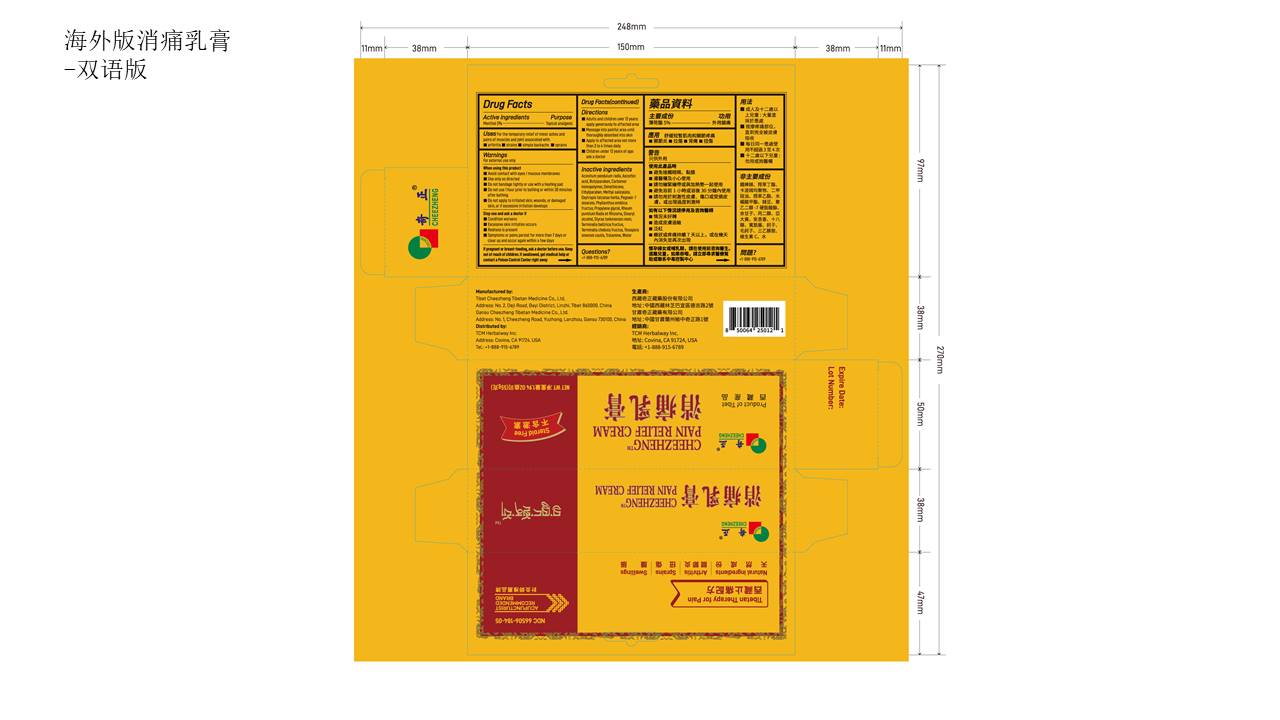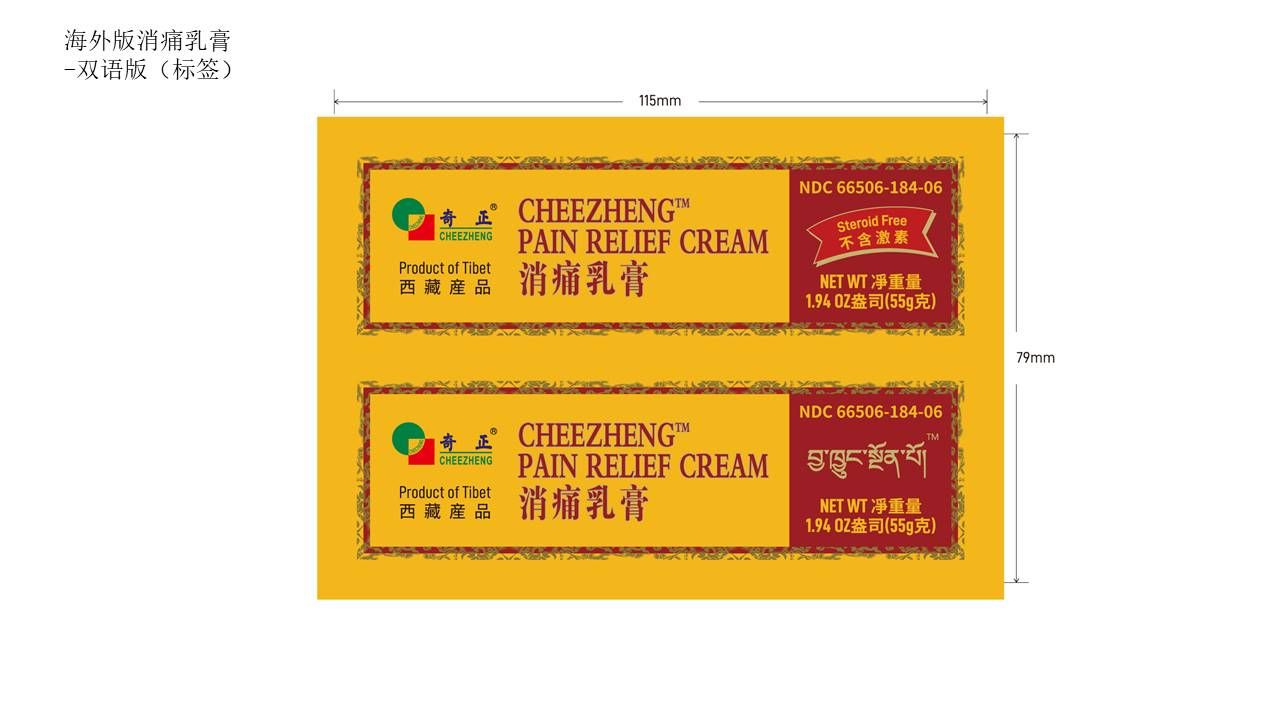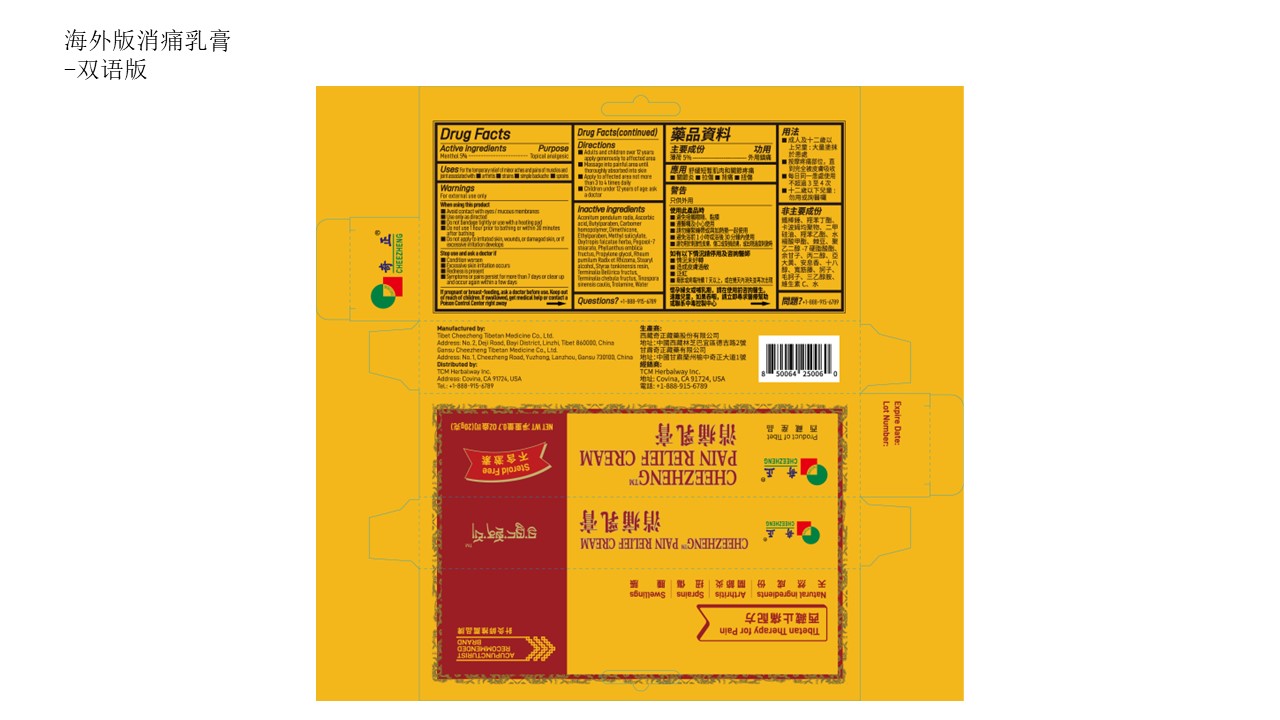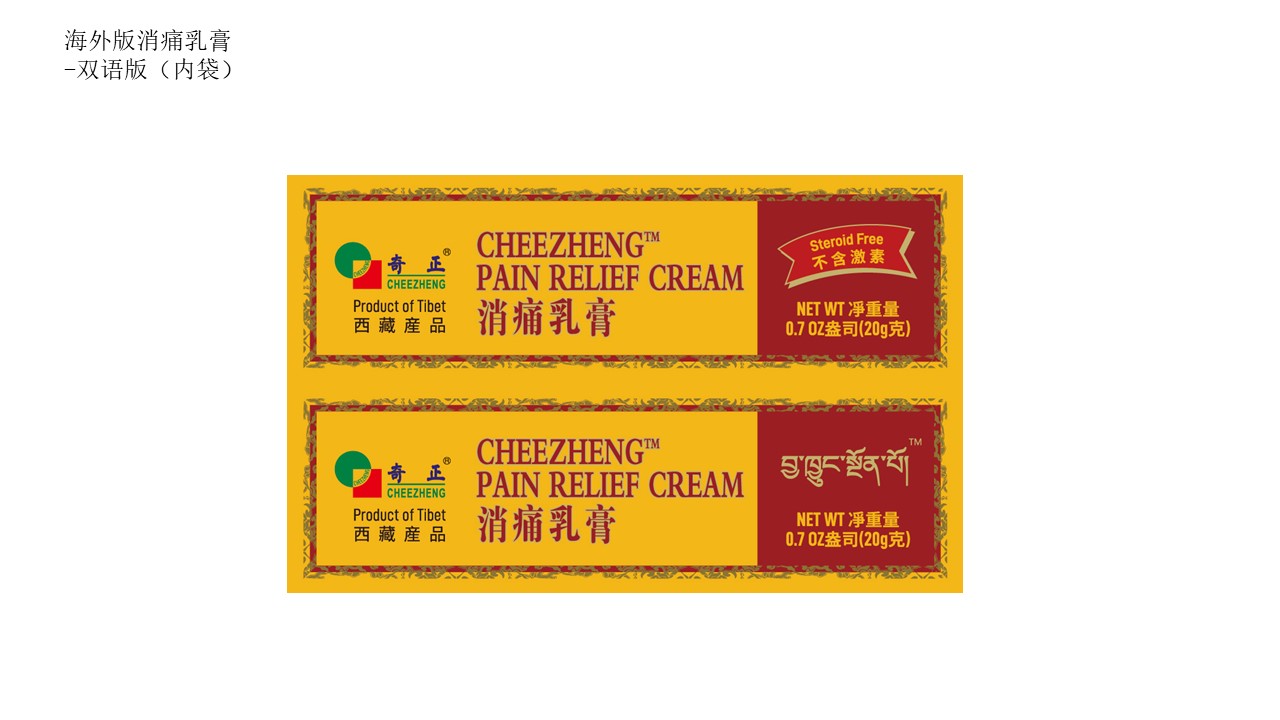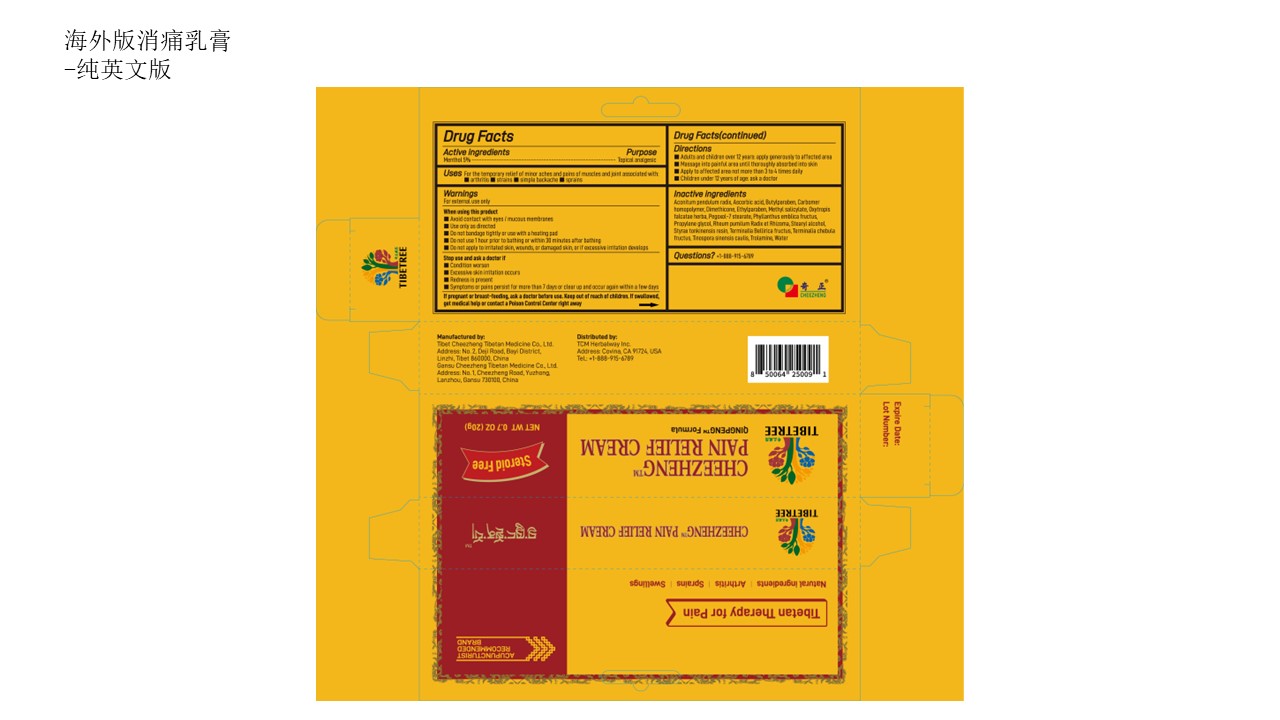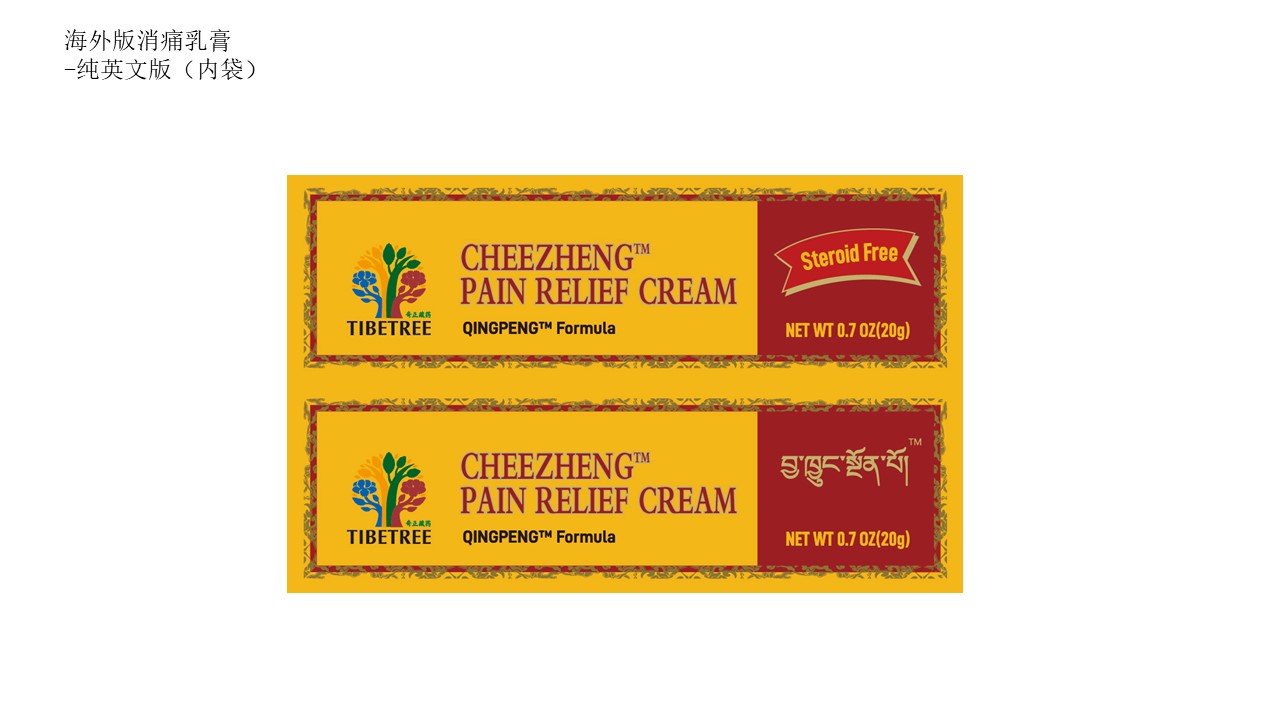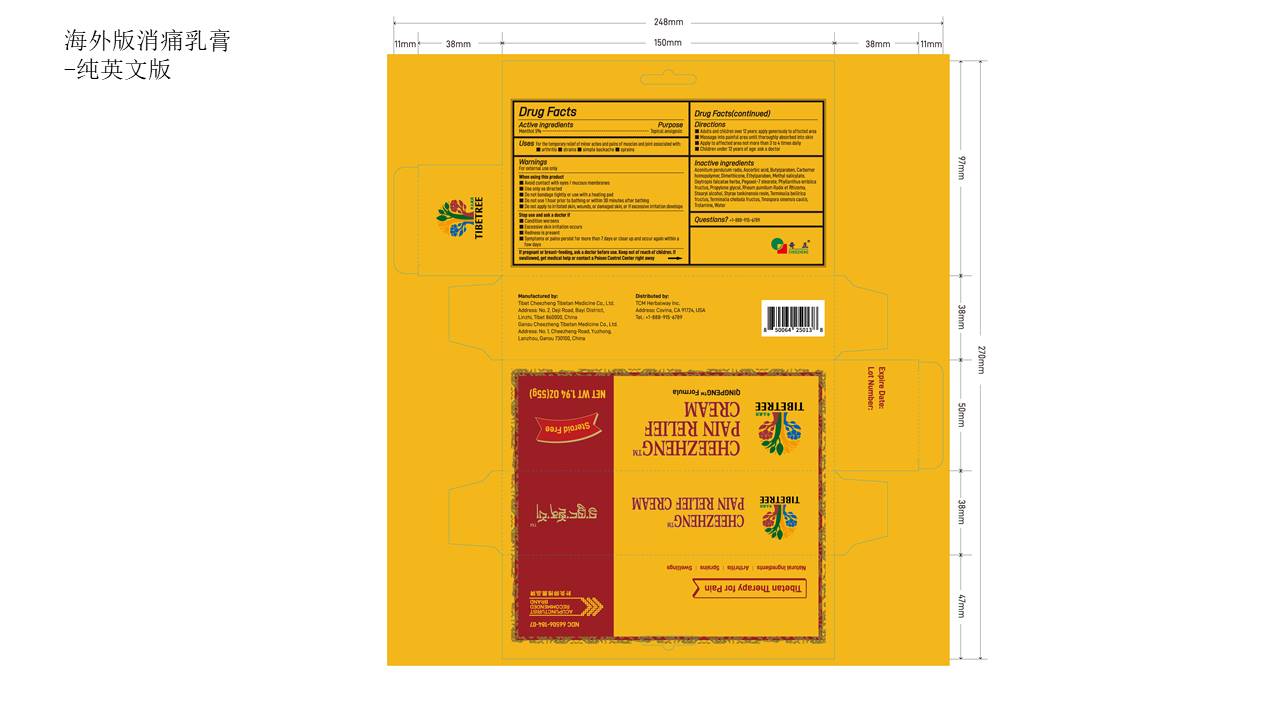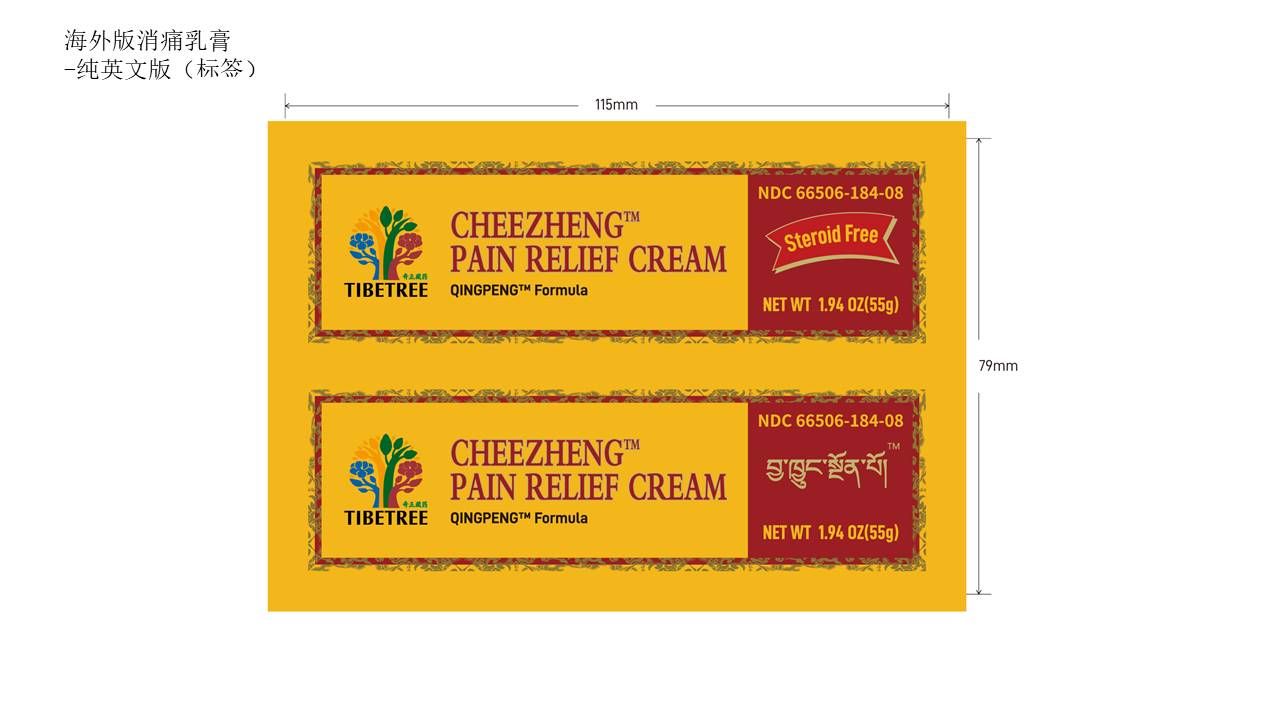 DRUG LABEL: Cheezheng Pain Relief Cream
NDC: 66506-184 | Form: CREAM
Manufacturer: Tibet Cheezheng Tibetan Medicine Co. Ltd
Category: otc | Type: HUMAN OTC DRUG LABEL
Date: 20240807

ACTIVE INGREDIENTS: MENTHOL 5 g/100 g
INACTIVE INGREDIENTS: ACONITUM PENDULUM ROOT; BUTYLPARABEN; CARBOMER HOMOPOLYMER, UNSPECIFIED TYPE; DIMETHICONE; ETHYLPARABEN; METHYL SALICYLATE; OXYTROPIS FALCATA WHOLE; PEGOXOL 7 STEARATE; PHYLLANTHUS EMBLICA FRUIT; PROPYLENE GLYCOL; RHEUM PUMILUM WHOLE; STEARYL ALCOHOL; STYRAX TONKINENSIS RESIN; TERMINALIA CHEBULA FRUIT; TERMINALIA BELLIRICA FRUIT; TINOSPORA SINENSIS STEM; TROLAMINE; ASCORBIC ACID; WATER

Cheezheng Pain Relief Cream

Active ingredients

Menthol 5%................……….…….Topical analgesic

Keep out of reach of children. If swallowed, get medical help or contact a Poison Control Center right away

If pregnant or breast-feeding, ask a doctor before use.

Directions

- Adults and children over 12 years: apply generously to affected area
- Massage into painful area until thoroughly absorbed into skin
- Apply to affected area not more than 3 to 4 times daily
- Children under 12 years of age: ask a doctor.

Inactive ingredients

Aconitum pendulum radix, Ascorbic acid, Butylparaben, Carbomer homopolymer, Dimethicone, Ethylparaben, Methyl salicylate, Oxytropis falcatae herba, Pegoxol-7 stearate, Phyllanthus emblica fructus, Propylene glycol, Rheum pumilum Radix et Rhizoma, Stearyl alcohol, Styrax tonkinensis resin, Terminalia bellirica fructus,Terminalia chebula fructus, Tinospora sinensis caulis, Trolamine, Water

Questions?

1-888-915-6789

Purpose

Topical analgesic

- Do not use 1 hour prior to bathing or within 30 minutes after bathing
- Do not apply to irritated skin, wounds, or damaged skin, or if excessive irritation develops

When using this product

- Avoid contact with eyes/mucous membranes
- Use only as directed
- Do not bandage tightly or use with a heating pad
- Do not use 1 hour prior to bathing or within 30 minutes after bathing
- Do not apply to irritated skin, wounds, or damaged skin, or if excessive irritation develops

Stop use and ask a doctor if

- Condition worsens
- Excessive skin irritation occurs
- Redness is present
- Symptoms or pains persist for more than 7 days or clear up and occur again within a few days

Uses

For the temporary relief of minor aches and pains of muscles and joint associated with:

arthritis
strains
simple backache
sprains

Warnings

For external use only